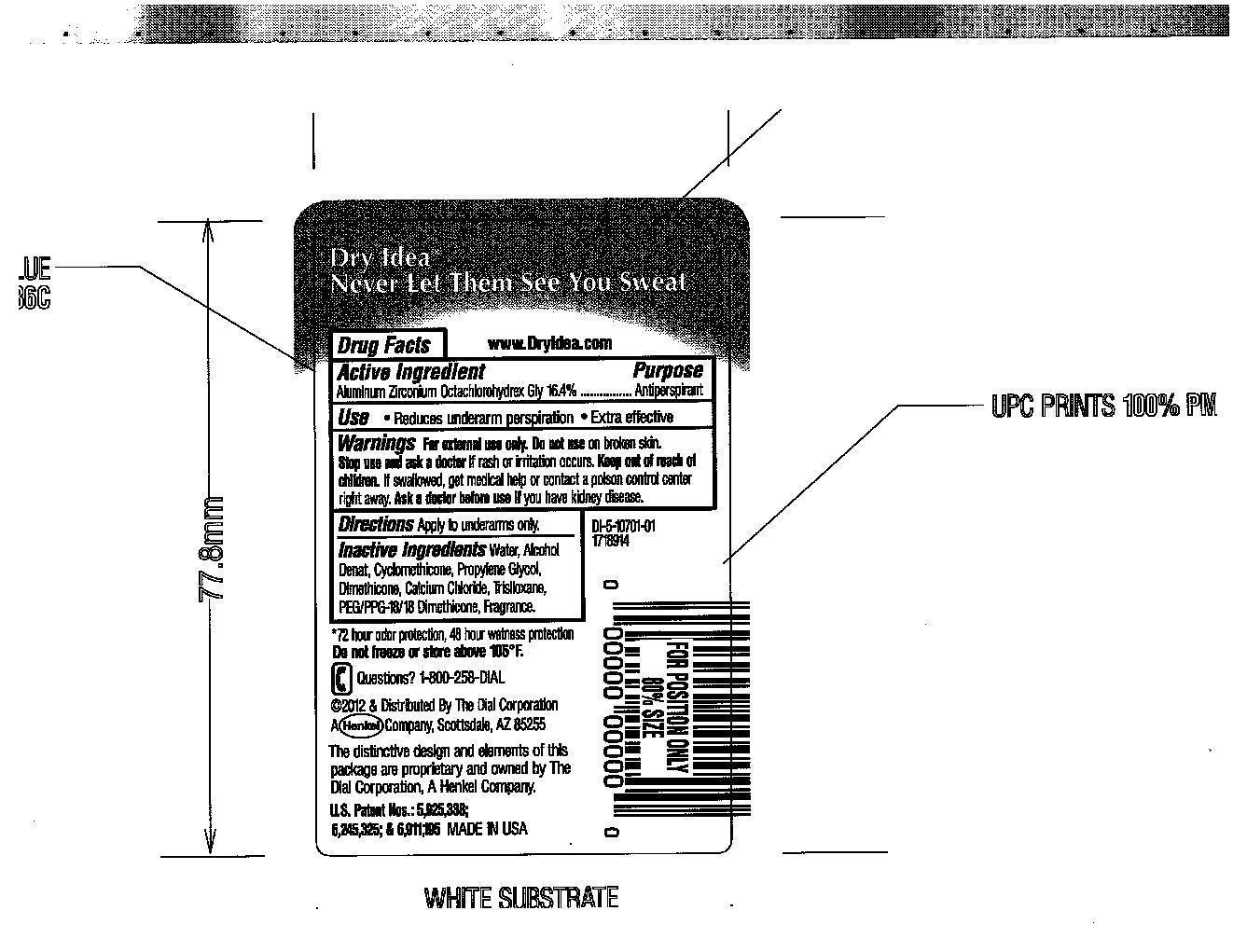 DRUG LABEL: Dry Idea Advanced Dry
NDC: 51815-218 | Form: Stick
Manufacturer: VVF Illinois Services LLC
Category: otc | Type: HUMAN OTC DRUG LABEL
Date: 20140317

ACTIVE INGREDIENTS: Aluminum Zirconium Octachlorohydrex GLY 13.94 g/85 g
INACTIVE INGREDIENTS: Water; ALCOHOL; CYCLOMETHICONE; PROPYLENE GLYCOL; DIMETHICONE; CALCIUM CHLORIDE; TRISILOXANE; PEG/PPG-18/18 DIMETHICONE

Dry Idea advanced dry fresh

Active Ingredient

Aluminum Zirconium Octachlorohydrex GLY 16.4%

Purpose

Antiperspirant

Warnings

For external use only
Do not use on broken skin

Stop use and ask a doctor if rash or irritation occurs

Keep out of reach of children

If swallowed, get medical help or contact a poison control center right away

uses

Reduces underarm perspiration

Ask a doctor before use if you have kidney disease

Inactive Ingredients

Water, Alcohol Denat, Cyclomethicone, Propylene Glycol, Dimethicone, Calcium Chloride, Trisiloxane, PEG/PPG-18/18 Dimethicone, Fragrance.

Questions?

1800-258-DIAL

Directions

Apply to underarms only